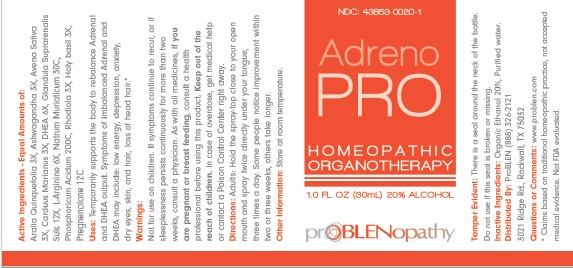 DRUG LABEL: Adrenal and DHEA
NDC: 43853-0020 | Form: LIQUID
Manufacturer: ProBLEN
Category: homeopathic | Type: HUMAN OTC DRUG LABEL
Date: 20211022

ACTIVE INGREDIENTS: AMERICAN GINSENG 3 [hp_X]/30 mL; WITHANIA SOMNIFERA ROOT 3 [hp_X]/30 mL; AVENA SATIVA FLOWERING TOP 3 [hp_X]/30 mL; MILK THISTLE 3 [hp_X]/30 mL; PRASTERONE 6 [hp_X]/30 mL; SUS SCROFA ADRENAL GLAND 12 [hp_X]/30 mL; ARGININE 6 [hp_X]/30 mL; SODIUM CHLORIDE 30 [hp_C]/30 mL; PHOSPHORIC ACID 200 [hp_C]/30 mL; RHODIOLA KIRILOWII ROOT 3 [hp_X]/30 mL
INACTIVE INGREDIENTS: ALCOHOL; WATER

Adrenal and DHEA

ACTIVE INGREDIENT

Active Ingredients Equal Parts Of: Aralia Quinquefolia 3X, Ashwagandha 3X, Avena Sativa 3X, Carduus Marianus 3X, DHEA 6X, Glandula Suprarenalis Suis 12X, L-Arginine 6X, Natrum Muriaticum 30C, Phosphoricum Acidum 200C, Rhadiola 3X. Holy basil 3X, Pregnenolone 12C.

*Claims based on traditional homeopathic practice, not accepted medical evidence. Not FDA evaluated.

INDICATIONS AND USAGE

Uses: Temporarily supports the body to rebalance Adrenal and DHEA output. Symptoms of imbalanced Adrenal and DHEA may include: low energy, depression, anxiety, dry eyes, skin, and hair, loss of head hair.*

WARNINGS

Warnings: Not for use on children. If symptoms continue recur, or if sleeplessness persists continuously for more than two weeks, consult a physician. As with all medicines, if you are pregnant or breast feeding, consult a health professional before using this product. Keep out of the reach of children.In case of overdose, get medical help or contact a Poison Control Center right away.

Keep out of the reach of children.

DOSAGE AND ADMINISTRATION

Directions: Adults: Hold the spray-top close to your open mouth and spray twice directly under your tongue, three times a day. Some people notice improvement within two or three weeks, others take longer.

Other Information: Store at room temperature.

Tamper Evident: There is a seal around the neck of the bottle.

Do not use if the seal is broken or missing.

Inactive Ingredients: Organic Ethanol 20%, Purified water.

QUESTIONS

Distributed By: ProBLEN (888) 326-2121

3021 Ridge Rd., Rockwall, TX 75032

Questions or Comments: www.problen.com

PACKAGE LABEL

NDC: 43853-0020-1

Adreno PRO

HOMEOPATHIC ORGANOTHERAPY

1.0 FL OZ (30ML) 20% ALCOHOL

PURPOSE

Temporarily supports the body to rebalance Adrenal and DHEA output. Symptoms of imbalanced Adrenal and DHEA may include: low energy, depression, anxiety, dry eyes, skin, and hair, loss of head hair.*